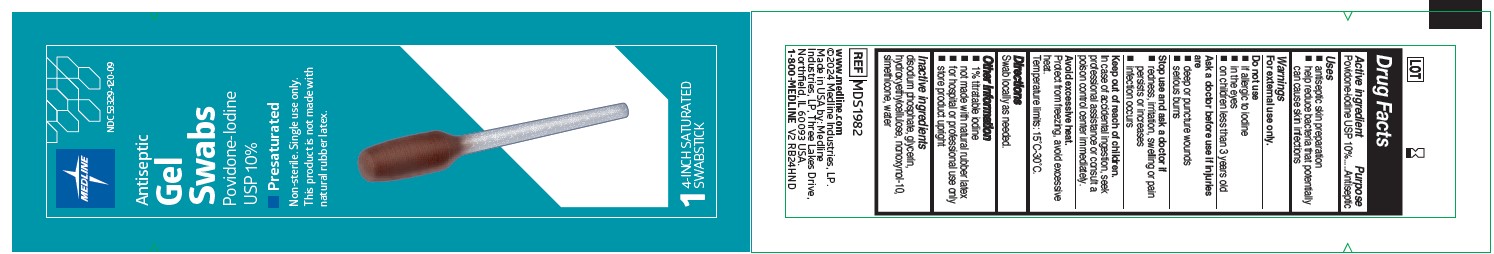 DRUG LABEL: Medline
NDC: 53329-120 | Form: SWAB
Manufacturer: Medline Industries, LP
Category: otc | Type: HUMAN OTC DRUG LABEL
Date: 20240701

ACTIVE INGREDIENTS: POVIDONE-IODINE 10 mg/1 mL
INACTIVE INGREDIENTS: NONOXYNOL-10; SODIUM PHOSPHATE, DIBASIC, ANHYDROUS; HYDROXYETHYL CELLULOSE, UNSPECIFIED; DIMETHICONE, UNSPECIFIED; GLYCERIN; WATER

120 Antiseptic Gel Swabs Povidone-Iodine USP 10%

Active Ingredient

Povidone-iodine USP 10%

Purpose

Antiseptic

Uses

- antiseptic skin preparation
- help reduce bacteria that potentially can cause skin infections

Warnings

For external use only.

Do not use

- if allergic to iodine
- in the eyes
- on children less than 3 years old

Ask a doctor before use if injuries are

- deep or puncture wounds
- serious burns

Keep out of reach of children.

In case of accidental ingestion, seek professional assistance or consult a poison control center immediately.

Avoid excessive heat.

Protect from freezing, avoid excessive heat.

Temperature limits: 15˚C-30˚C.

Stop use and ask a doctor if

- redness, irritation, swelling or pain persists or increases
- infection occurs

Directions

Swab locally as needed.

Other information

- 1% titratable iodine
- not made with natural rubber latex
- for hospital or professional use only
- store product upright

Inactive ingredients

disodium phosphate, glycerin, hydroxyethylcellulose, nonoxynol-10, simethicone, water

Manufacturing Information

Made in USA by: Medline Industries, LP

Three Lakes Drive,
Northfield, IL 60093 USA.

REF: MDS1982

1-800-MEDLINE V2 RB24HND

www.medline.com